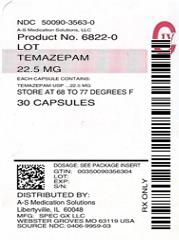 DRUG LABEL: TEMAZEPAM
NDC: 50090-3563 | Form: CAPSULE
Manufacturer: A-S Medication Solutions
Category: prescription | Type: HUMAN PRESCRIPTION DRUG LABEL
Date: 20200118
DEA Schedule: CIV

ACTIVE INGREDIENTS: TEMAZEPAM 22.5 mg/1 1
INACTIVE INGREDIENTS: FD&C BLUE NO. 1; FD&C RED NO. 3; GELATIN, UNSPECIFIED; LACTOSE MONOHYDRATE; MAGNESIUM STEARATE; FERRIC OXIDE RED; TITANIUM DIOXIDE; BUTYL ALCOHOL; SHELLAC; ALUMINUM OXIDE; ISOPROPYL ALCOHOL; PROPYLENE GLYCOL; ALCOHOL; ETHYL ACETATE

Temazepam
Capsules USP
CIV
Rx only

WARNING: RISKS FROM CONCOMITANT USE WITH OPIOIDS

Concomitant use of benzodiazepines and opioids may result in profound sedation, respiratory depression, coma, and death (see WARNINGS and Drug Interactions).

• Reserve concomitant prescribing of these drugs for use in patients for whom alternative treatment options are inadequate.
• Limit dosages and durations to the minimum required.
• Follow patients for signs and symptoms of respiratory depression and sedation.

DESCRIPTION

Temazepam Capsules USP are benzodiazepine hypnotic agents. The chemical name is 7-chloro-1,3-dihydro-3-hydroxy-1-methyl-5-phenyl-2H-1,4-benzodiazepin-2-one, and the structural formula is:

Temazepam is a white, crystalline substance, very slightly soluble in water and sparingly soluble in alcohol USP.

Temazepam Capsules USP, 7.5 mg, 15 mg, 22.5 mg, and 30 mg, are for oral administration.

7.5 mg, 15 mg, 22.5 mg, and 30 mg Capsules

Active Ingredient: temazepam USP

7.5 mg Capsules

Inactive Ingredients: FD&C Blue #1, FD&C Red #3, gelatin, lactose, magnesium stearate, red iron oxide, titanium dioxide.

May also include: n-butyl alcohol, iron oxide red, shellac, shellac glaze, SD-35A alcohol.

15 mg Capsules

Inactive Ingredients: FD&C Blue #1, FD&C Red #3, gelatin, lactose, magnesium stearate, red iron oxide, titanium dioxide.

May also include: n-butyl alcohol, FD&C Blue #1/Brilliant Blue FCF Aluminum Lake, iron oxide red, isopropyl alcohol, propylene glycol, shellac, shellac glaze, SD-35A alcohol, SD-45 alcohol.

22.5 mg Capsules

Inactive Ingredients: FD&C Blue #1, FD&C Red #3, gelatin, lactose, magnesium stearate, red iron oxide, titanium dioxide.

May also include: n-butyl alcohol, FD&C Blue #1/Brilliant Blue FCF Aluminum Lake, iron oxide red, isopropyl alcohol, propylene glycol, shellac, shellac glaze, SD-35A alcohol, SD-45 alcohol.

30 mg Capsules

Inactive Ingredients: FD&C Blue #1, FD&C Red #3, gelatin, lactose, magnesium stearate, red iron oxide, titanium dioxide.

May also include: n-butyl alcohol, FD&C Blue #1/Brilliant Blue FCF Aluminum Lake, iron oxide red, isopropyl alcohol, propylene glycol, shellac, shellac glaze, SD-35A alcohol, SD-45 alcohol.

CLINICAL PHARMACOLOGY

Pharmacokinetics

In a single and multiple dose absorption, distribution, metabolism, and excretion (ADME) study, using ^3H labeled drug, Restoril (temazepam) was well absorbed and found to have minimal (8%) first pass metabolism. There were no active metabolites formed and the only significant metabolite present in blood was the O-conjugate. The unchanged drug was 96% bound to plasma proteins. The blood level decline of the parent drug was biphasic with the short half-life ranging from 0.4 to 0.6 hours and the terminal half-life from 3.5 to 18.4 hours (mean 8.8 hours), depending on the study population and method of determination. Metabolites were formed with a half-life of 10 hours and excreted with a half-life of approximately 2 hours. Thus, formation of the major metabolite is the rate limiting step in the biodisposition of temazepam. There is no accumulation of metabolites. A dose-proportional relationship has been established for the area under the plasma concentration/time curve over the 15 to 30 mg dose range.

Temazepam was completely metabolized through conjugation prior to excretion; 80% to 90% of the dose appeared in the urine. The major metabolite was the O-conjugate of temazepam (90%); the O-conjugate of N-desmethyl temazepam was a minor metabolite (7%).

Bioavailability, Induction, and Plasma Levels

Following ingestion of a 30 mg Restoril capsule, measurable plasma concentrations were achieved 10 to 20 minutes after dosing with peak plasma levels ranging from 666 to 982 ng/mL (mean 865 ng/mL) occurring approximately 1.2 to 1.6 hours (mean 1.5 hours) after dosing.

In a 7 day study, in which subjects were given a 30 mg Restoril capsule 1 hour before retiring, steady-state (as measured by the attainment of maximal trough concentrations) was achieved by the third dose. Mean plasma levels of temazepam (for days 2 to 7) were 260±210 ng/mL at 9 hours and 75±80 ng/mL at 24 hours after dosing. A slight trend toward declining 24 hour plasma levels was seen after day 4 in the study, however, the 24 hour plasma levels were quite variable.

At a dose of 30 mg once-a-day for 8 weeks, no evidence of enzyme induction was found in man.

Elimination Rate of Benzodiazepine Hypnotics and Profile of Common Untoward Effects

The type and duration of hypnotic effects and the profile of unwanted effects during administration of benzodiazepine hypnotics may be influenced by the biologic half-life of the administered drug and for some hypnotics, the half-life of any active metabolites formed. Benzodiazepine hypnotics have a spectrum of half-lives from short (<4 hours) to long (>20 hours). When half-lives are long, drug (and for some drugs their active metabolites) may accumulate during periods of nightly administration and be associated with impairments of cognitive and/or motor performance during waking hours; the possibility of interaction with other psychoactive drugs or alcohol will be enhanced. In contrast, if half-lives are shorter, drug (and, where appropriate, its active metabolites) will be cleared before the next dose is ingested, and carry-over effects related to excessive sedation or CNS depression should be minimal or absent. However, during nightly use for an extended period, pharmacodynamic tolerance or adaptation to some effects of benzodiazepine hypnotics may develop. If the drug has a short elimination half-life, it is possible that a relative deficiency of the drug, or, if appropriate, its active metabolites (i.e., in relationship to the receptor site) may occur at some point in the interval between each night's use. This sequence of events may account for 2 clinical findings reported to occur after several weeks of nightly use of rapidly eliminated benzodiazepine hypnotics, namely, increased wakefulness during the last third of the night, and the appearance of increased signs of daytime anxiety.

Controlled Trials Supporting Efficacy

Restoril improved sleep parameters in clinical studies. Residual medication effects (“hangover”) were essentially absent. Early morning awakening, a particular problem in the geriatric patient, was significantly reduced.

Patients with chronic insomnia were evaluated in 2 week, placebo controlled sleep laboratory studies with Restoril at doses of 7.5 mg, 15 mg, and 30 mg, given 30 minutes prior to bedtime. There was a linear dose-response improvement in total sleep time and sleep latency, with significant drug-placebo differences at 2 weeks occurring only for total sleep time at the 2 higher doses, and for sleep latency only at the highest dose.

In these sleep laboratory studies, REM sleep was essentially unchanged and slow wave sleep was decreased. No measurable effects on daytime alertness or performance occurred following Restoril treatment or during the withdrawal period, even though a transient sleep disturbance in some sleep parameters was observed following withdrawal of the higher doses. There was no evidence of tolerance development in the sleep laboratory parameters when patients were given Restoril nightly for at least 2 weeks.

In addition, normal subjects with transient insomnia associated with first night adaptation to the sleep laboratory were evaluated in 24 hour, placebo controlled sleep laboratory studies with Restoril at doses of 7.5 mg, 15 mg, and 30 mg, given 30 minutes prior to bedtime. There was a linear dose-response improvement in total sleep time, sleep latency and number of awakenings, with significant drug-placebo differences occurring for sleep latency at all doses, for total sleep time at the 2 higher doses and for number of awakenings only at the 30 mg dose.

INDICATIONS AND USAGE

Temazepam Capsules USP are indicated for the short-term treatment of insomnia (generally 7 to 10 days).

For patients with short-term insomnia, instructions in the prescription should indicate that Temazepam Capsules USP should be used for short periods of time (7 to 10 days).

The clinical trials performed in support of efficacy were 2 weeks in duration with the final formal assessment of sleep latency performed at the end of treatment.

CONTRAINDICATIONS

Benzodiazepines may cause fetal harm when administered to a pregnant woman. An increased risk of congenital malformations associated with the use of diazepam and chlordiazepoxide during the first trimester of pregnancy has been suggested in several studies. Transplacental distribution has resulted in neonatal CNS depression following the ingestion of therapeutic doses of a benzodiazepine hypnotic during the last weeks of pregnancy.

Reproduction studies in animals with temazepam were performed in rats and rabbits. In a perinatal-postnatal study in rats, oral doses of 60 mg/kg/day resulted in increasing nursling mortality. Teratology studies in rats demonstrated increased fetal resorptions at doses of 30 and 120 mg/kg in one study and increased occurrence of rudimentary ribs, which are considered skeletal variants, in a second study at doses of 240 mg/kg or higher. In rabbits, occasional abnormalities such as exencephaly and fusion or asymmetry of ribs were reported without dose relationship. Although these abnormalities were not found in the concurrent control group, they have been reported to occur randomly in historical controls. At doses of 40 mg/kg or higher, there was an increased incidence of the 13th rib variant when compared to the incidence in concurrent and historical controls.

Temazepam capsules are contraindicated in women who are or may become pregnant. If this drug is used during pregnancy, or if the patient becomes pregnant while taking this drug, the patient should be apprised of the potential hazard to the fetus. Patients should be instructed to discontinue the drug prior to becoming pregnant. The possibility that a woman of childbearing potential may be pregnant at the time of institution of therapy should be considered.

WARNINGS

Concomitant use of benzodiazepines, including temazepam capsules, and opioids may result in profound sedation, respiratory depression, coma, and death. Because of these risks, reserve concomitant prescribing of these drugs for use in patients for whom alternative treatment options are inadequate.

Observational studies have demonstrated that concomitant use of opioid analgesics and benzodiazepines increases the risk of drug-related mortality compared to use of opioids alone. If a decision is made to prescribe temazepam capsules concomitantly with opioids, prescribe the lowest effective dosages and minimum durations of concomitant use, and follow patients closely for signs and symptoms of respiratory depression and sedation. In patients already receiving an opioid analgesic, prescribe a lower initial dose of temazepam capsules than indicated in the absence of an opioid and titrate based on clinical response. If an opioid is initiated in a patient already taking temazepam capsules, prescribe a lower initial dose of the opioid and titrate based upon clinical response.

Advise both patients and caregivers about the risks of respiratory depression and sedation when temazepam capsules are used with opioids. Advise patients not to drive or operate heavy machinery until the effects of concomitant use with the opioid have been determined (see Drug Interactions).

Sleep disturbance may be the presenting manifestation of an underlying physical and/or psychiatric disorder. Consequently, a decision to initiate symptomatic treatment of insomnia should only be made after the patient has been carefully evaluated. The failure of insomnia to remit after 7 to 10 days of treatment may indicate the presence of a primary psychiatric and/or medical illness that should be evaluated. Worsening of insomnia may be the consequence of an unrecognized psychiatric or physical disorder as may the emergence of new abnormalities of thinking or behavior. Such abnormalities have also been reported to occur in association with the use of drugs with central nervous system depressant activity, including those of the benzodiazepine class. Because some of the worrisome adverse effects of benzodiazepines, including temazepam capsules, appear to be dose related (see PRECAUTIONS and DOSAGE AND ADMINISTRATION), it is important to use the lowest possible effective dose. Elderly patients are especially at risk.

Some of these changes may be characterized by decreased inhibition, e.g., aggressiveness and extroversion that seem out of character, similar to that seen with alcohol. Other kinds of behavioral changes can also occur, for example, bizarre behavior, agitation, hallucinations, and depersonalization. Complex behaviors such as “sleep-driving” (i.e., driving while not fully awake after ingestion of a sedative-hypnotic, with amnesia for the event) have been reported. These events can occur in sedative-hypnotic-naïve as well as in sedative-hypnotic-experienced persons. Although behaviors such as “sleep-driving” may occur with temazepam capsules alone at therapeutic doses, the use of alcohol and other CNS depressants with temazepam capsules appear to increase the risk of such behaviors, as does the use of temazepam capsules at doses exceeding the maximum recommended dose. Due to the risk to the patient and the community, discontinuation of temazepam capsules should be strongly considered for patients who report a “sleep-driving” episode. Other complex behaviors (e.g., preparing and eating food, making phone calls, or having sex) have been reported in patients who are not fully awake after taking a sedative-hypnotic. As with “sleep-driving”, patients usually do not remember these events. Amnesia and other neuro-psychiatric symptoms may occur unpredictably. In primarily depressed patients, worsening of depression, including suicidal thinking has been reported in association with the use of sedative/hypnotics.

It can rarely be determined with certainty whether a particular instance of the abnormal behaviors listed above is drug induced, spontaneous in origin, or a result of an underlying psychiatric or physical disorder. Nonetheless, the emergence of any new behavioral sign or symptom of concern requires careful and immediate evaluation.

Withdrawal symptoms (of the barbiturate type) have occurred after the abrupt discontinuation of benzodiazepines (see DRUG ABUSE AND DEPENDENCE).

Because temazepam capsules can cause drowsiness and a decreased level of consciousness, patients, particularly the elderly, are at higher risk of falls.

Severe Anaphylactic and Anaphylactoid Reactions

Rare cases of angioedema involving the tongue, glottis or larynx have been reported in patients after taking the first or subsequent doses of sedative-hypnotics, including temazepam capsules. Some patients have had additional symptoms such as dyspnea, throat closing, or nausea and vomiting that suggest anaphylaxis. Some patients have required medical therapy in the emergency department. If angioedema involves the tongue, glottis or larynx, airway obstruction may occur and be fatal. Patients who develop angioedema after treatment with temazepam capsules should not be rechallenged with the drug.

PRECAUTIONS

General

Since the risk of the development of oversedation, dizziness, confusion, and/or ataxia increases substantially with larger doses of benzodiazepines in elderly and debilitated patients, 7.5 mg of temazepam capsules are recommended as the initial dosage for such patients.

Temazepam capsules should be administered with caution in severely depressed patients or those in whom there is any evidence of latent depression; it should be recognized that suicidal tendencies may be present and protective measures may be necessary.

The usual precautions should be observed in patients with impaired renal or hepatic function and in patients with chronic pulmonary insufficiency.

If temazepam capsules are to be combined with other drugs having known hypnotic properties or CNS-depressant effects, consideration should be given to potential additive effects.

The possibility of a synergistic effect exists with the co-administration of temazepam capsules and diphenhydramine. One case of stillbirth at term has been reported 8 hours after a pregnant patient received temazepam capsules and diphenhydramine. A cause and effect relationship has not yet been determined (see CONTRAINDICATIONS).

Information for Patients

The text of a patient Medication Guide is printed at the end of this insert. To assure safe and effective use of temazepam capsules, the information and instructions provided in this patient Medication Guide should be discussed with patients.

Special Concerns

“Sleep-Driving” and Other Complex Behaviors – There have been reports of people getting out of bed after taking a sedative-hypnotic and driving their cars while not fully awake, often with no memory of the event. If a patient experiences such an episode, it should be reported to his or her doctor immediately, since “sleep-driving” can be dangerous. This behavior is more likely to occur when temazepam capsules are taken with alcohol or other central nervous system depressants (see WARNINGS). Other complex behaviors (e.g., preparing and eating food, making phone calls, or having sex) have been reported in patients who are not fully awake after taking a sedative-hypnotic. As with “sleep-driving”, patients usually do not remember these events.

Advise patients that increased drowsiness and decreased consciousness may increase the risk of falls in some patients.

Laboratory Tests

The usual precautions should be observed in patients with impaired renal or hepatic function and in patients with chronic pulmonary insufficiency. Abnormal liver function tests as well as blood dyscrasias have been reported with benzodiazepines.

Drug Interactions

The concomitant use of benzodiazepines and opioids increases the risk of respiratory depression because of actions at different receptor sites in the CNS that control respiration. Benzodiazepines interact at GABAA sites and opioids interact primarily at mu receptors. When benzodiazepines and opioids are combined, the potential for benzodiazepines to significantly worsen opioid-related respiratory depression exists. Limit dosage and duration of concomitant use of benzodiazepines and opioids, and monitor patients closely for respiratory depression and sedation.

The pharmacokinetic profile of temazepam does not appear to be altered by orally administered cimetidine dosed according to labeling.

Carcinogenesis, Mutagenesis, Impairment of Fertility

Carcinogenicity studies were conducted in rats at dietary temazepam doses up to 160 mg/kg/day for 24 months and in mice at dietary doses of 160 mg/kg/day for 18 months. No evidence of carcinogenicity was observed although hyperplastic liver nodules were observed in female mice exposed to the highest dose. The clinical significance of this finding is not known.

Fertility in male and female rats was not adversely affected by temazepam capsules.

No mutagenicity tests have been done with temazepam.

Pregnancy

Pregnancy Category X (see CONTRAINDICATIONS).

Nursing Mothers

It is not known whether this drug is excreted in human milk. Because many drugs are excreted in human milk, caution should be exercised when temazepam capsules are administered to a nursing woman.

Pediatric Use

Safety and effectiveness in pediatric patients have not been established.

Geriatric Use

Clinical studies of Restoril did not include sufficient numbers of subjects aged 65 and over to determine whether they respond differently from younger subjects. Other reported clinical experience has not identified differences in response between the elderly and younger patients. In general, dose selection for an elderly patient should be cautious, usually starting at the low end of the dosing range, reflecting the greater frequency of decreased hepatic, renal, or cardiac function, and of concomitant disease or other drug therapy commonly observed in this population. Temazepam capsules 7.5 mg is recommended as the initial dosage for patients aged 65 and over since the risk of the development of oversedation, dizziness, confusion, ataxia and/or falls increases substantially with larger doses of benzodiazepines in elderly and debilitated patients.

ADVERSE REACTIONS

During controlled clinical studies in which 1076 patients received temazepam capsules at bedtime, the drug was well tolerated. Side effects were usually mild and transient. Adverse reactions occurring in 1% or more of patients are presented in the following table:

 | Temazepam Capsules % Incidence (n=1076) | Placebo % Incidence (n=783)
Drowsiness | 9.1 | 5.6
Headache | 8.5 | 9.1
Fatigue | 4.8 | 4.7
Nervousness | 4.6 | 8.2
Lethargy | 4.5 | 3.4
Dizziness | 4.5 | 3.3
Nausea | 3.1 | 3.8
Hangover | 2.5 | 1.1
Anxiety | 2.0 | 1.5
Depression | 1.7 | 1.8
Dry Mouth | 1.7 | 2.2
Diarrhea | 1.7 | 1.1
Abdominal Discomfort | 1.5 | 1.9
Euphoria | 1.5 | 0.4
Weakness | 1.4 | 0.9
Confusion | 1.3 | 0.5
Blurred Vision | 1.3 | 1.3
Nightmares | 1.2 | 1.7
Vertigo | 1.2 | 0.8

The following adverse events have been reported less frequently (0.5% to 0.9%):

Central Nervous System – anorexia, ataxia, equilibrium loss, tremor, increased dreaming

Cardiovascular – dyspnea, palpitations

Gastrointestinal – vomiting

Musculoskeletal – backache

Special Senses – hyperhidrosis, burning eyes

Amnesia, hallucinations, horizontal nystagmus, and paradoxical reactions including restlessness, overstimulation and agitation were rare (less than 0.5%).

DRUG ABUSE AND DEPENDENCE

Abuse and addiction are separate and distinct from physical dependence and tolerance. Abuse is characterized by misuse of the drug for non-medical purposes, often in combination with other psychoactive substances. Physical dependence is a state of adaptation that is manifested by a specific withdrawal syndrome that can be produced by abrupt cessation, rapid dose reduction, decreasing blood level of the drug and/or administration of an antagonist. Tolerance is a state of adaptation in which exposure to a drug induces changes that result in a diminution of one or more of the drug's effects over time. Tolerance may occur to both the desired and undesired effects of drugs and may develop at different rates for different effects.

Addiction is a primary, chronic, neurobiological disease with genetic, psychosocial, and environmental factors influencing its development and manifestations. It is characterized by behaviors that include one or more of the following: impaired control over drug use, compulsive use, continued use despite harm, and craving. Drug addiction is a treatable disease, utilizing a multidisciplinary approach, but relapse is common.

Controlled Substance

Temazepam capsules are a controlled substance in Schedule IV.

Abuse and Dependence

Withdrawal symptoms, similar in character to those noted with barbiturates and alcohol (convulsions, tremor, abdominal, and muscle cramps, vomiting, and sweating), have occurred following abrupt discontinuance of benzodiazepines. The more severe withdrawal symptoms have usually been limited to those patients who received excessive doses over an extended period of time. Generally milder withdrawal symptoms (e.g., dysphoria and insomnia) have been reported following abrupt discontinuance of benzodiazepines taken continuously at therapeutic levels for several months. Consequently, after extended therapy at doses higher than 15 mg, abrupt discontinuation should generally be avoided and a gradual dosage tapering schedule followed. As with any hypnotic, caution must be exercised in administering temazepam capsules to individuals known to be addiction-prone or to those whose history suggests they may increase the dosage on their own initiative. It is desirable to limit repeated prescriptions without adequate medical supervision.

OVERDOSAGE

Manifestations of acute overdosage of temazepam capsules can be expected to reflect the CNS effects of the drug and include somnolence, confusion, and coma, with reduced or absent reflexes, respiratory depression, and hypotension. The oral LD50 of temazepam capsules were 1963 mg/kg in mice, 1833 mg/kg in rats, and >2400 mg/kg in rabbits.

Treatment

If the patient is conscious, vomiting should be induced mechanically or with emetics. Gastric lavage should be employed utilizing concurrently a cuffed endotracheal tube if the patient is unconscious to prevent aspiration and pulmonary complications. Maintenance of adequate pulmonary ventilation is essential. The use of pressor agents intravenously may be necessary to combat hypotension. Fluids should be administered intravenously to encourage diuresis. The value of dialysis has not been determined. If excitation occurs, barbiturates should not be used. It should be borne in mind that multiple agents may have been ingested. Flumazenil (Romazicon®)*, a specific benzodiazepine receptor antagonist, is indicated for the complete or partial reversal of the sedative effects of benzodiazepines and may be used in situations when an overdose with a benzodiazepine is known or suspected. Prior to the administration of flumazenil, necessary measures should be instituted to secure airway, ventilation, and intravenous access. Flumazenil is intended as an adjunct to, not as a substitute for, proper management of benzodiazepine overdose. Patients treated with flumazenil should be monitored for re-sedation, respiratory depression, and other residual benzodiazepine effects for an appropriate period after treatment. The prescriber should be aware of a risk of seizure in association with flumazenil treatment, particularly in long-term benzodiazepine users and in cyclic antidepressant overdose. The complete flumazenil package insert including CONTRAINDICATIONS, WARNINGS, and PRECAUTIONS should be consulted prior to use.

Up-to-date information about the treatment of overdose can often be obtained from a certified Regional Poison Control Center. Telephone numbers of certified Regional Poison Control Centers are listed in the Physicians' Desk Reference®**.

DOSAGE AND ADMINISTRATION

While the recommended usual adult dose is 15 mg before retiring, 7.5 mg may be sufficient for some patients, and others may need 30 mg. In transient insomnia, a 7.5 mg dose may be sufficient to improve sleep latency. In elderly or debilitated patients, it is recommended that therapy be initiated with 7.5 mg until individual responses are determined.

HOW SUPPLIED

Product: 50090-3563

NDC: 50090-3563-0 30 CAPSULE in a BOTTLE

MEDICATION GUIDE

Temazepam (te-maz'ĕ-pam) Capsules, C-IV

What is the most important information I should know about temazepam capsules?

- Temazepam capsules are a benzodiazepine medicine. Taking benzodiazepines with opioid medicines, alcohol, or other central nervous system depressants (including street drugs) can cause severe drowsiness, breathing problems (respiratory depression), coma and death.
- After taking temazepam capsules, you may get up out of bed while not being fully awake and do an activity that you do not know you are doing. The next morning, you may not remember that you did anything during the night. You have a higher chance for doing these activities if you drink alcohol or take other medicines that make you sleepy with temazepam capsules. Reported activities include:
  o driving a car (“sleep-driving”)
  o making and eating food
  o talking on the phone
  o having sex
  o sleep-walking

Call your healthcare provider right away if you find out that you have done any of the above activities after taking temazepam capsules.

- Do not take temazepam capsules unless you are able to stay in bed a full night (7 to 8 hours) before you must be active again.
- Do not take more temazepam capsules than prescribed.

What are temazepam capsules?

- Temazepam capsules are a prescription sleep medicine. Temazepam capsules are used in adults for the short-term (usually 7 to 10 days) treatment of a sleep problem called insomnia. Symptoms of insomnia include trouble falling asleep and waking up often during the night.
- Temazepam capsules are a federal controlled substance (C-IV) because it can be abused or lead to dependence. Keep temazepam capsules in a safe place to prevent misuse and abuse. Selling or giving away temazepam capsules may harm others, and is against the law. Tell your healthcare provider if you have ever abused or been dependent on alcohol, prescription medicines or street drugs.
- It is not known if temazepam capsules are safe and effective in children.
- It is not known if temazepam capsules are safe and effective for use longer than 2 weeks.

Do not take temazepam capsules if you:

- are allergic to temazepam or any of the ingredients in temazepam capsules. See the end of this Medication Guide for a complete list of ingredients in temazepam capsules.

Before you take temazepam capsules, tell your healthcare provider about all of your medical conditions, including if you:

- have a history of depression, mental illness or, suicidal thoughts
- have a history of drug or alcohol abuse or addiction
- have lung disease or breathing problems
- are pregnant or plan to become pregnant. Temazepam capsules may cause birth defects or harm your unborn baby.
- are breastfeeding, or plan to breastfeed. Temazepam capsules may pass through your breast milk and may harm your baby. Talk to your healthcare provider about the best way to feed your baby if you take temazepam capsules.

Tell your healthcare provider about all of the medicines you take, including prescription and over-the-counter medicines, vitamins, and herbal supplements.
Taking temazepam capsules with certain other medicines can cause side effects or affect how well temazepam capsules or the other medicines work. Do not start or stop other medicines without talking to your healthcare provider.
Do not take temazepam capsules with other medicines that can make you sleepy unless your healthcare provider tells you to.

How should I take temazepam capsules?

- See “What is the most important information I should know about temazepam capsules?”
- Take temazepam capsules exactly as your healthcare providers tell you to take it. Take temazepam capsules right before you get into bed.
- Do not take temazepam capsules unless you are able to get a full night’s sleep before you must be active again.
- If you take too much temazepam capsules or overdose, get emergency treatment right away.

What should I avoid while taking temazepam capsules?

- Do not drive, operate machinery, do other dangerous activities or do anything that needs you to be alert until you know how temazepam capsules affects you.
- You should not drink alcohol while you are taking temazepam capsules.

What are the possible side effects of temazepam capsules?

Temazepam capsules may cause serious side effects, including:

- See “What is the most important information I should know about temazepam capsules?”
- Withdrawal symptoms. You may have withdrawal symptoms if you stop taking temazepam capsules suddenly. Withdrawal symptoms can be serious and include seizures shakiness, stomach and muscle cramps, vomiting and sweating. Mild withdrawal symptoms include a depressed mood and trouble sleeping. Talk to your healthcare provider about slowly stopping temazepam capsules to avoid withdrawal symptoms.
- Abnormal thoughts and behavior. Symptoms include more outgoing or aggressive behavior than normal, confusion, agitation, hallucinations, worsening of depression, and suicidal thoughts.
- Abuse and dependence. Taking temazepam capsules can cause physical and psychological dependence. Physical and psychological dependence is not the same as drug addiction. Your healthcare provider can tell you more about the differences between physical and psychological dependence and drug addiction.
- Severe allergic reactions. Symptoms include swelling of the tongue or throat, trouble breathing, and nausea and vomiting. Get emergency medical help right away if you have these symptoms after taking temazepam capsules.

The most common side effects of temazepam capsules include:

- drowsiness
- headache
- tiredness
- nervousness
- dizziness
- nausea

You may still feel drowsy the next day after taking temazepam capsules. Do not drive or do other dangerous activities after taking temazepam capsules until you feel fully awake.
These are not all the possible side effects of temazepam capsules. Call your doctor for medical advice about side effects. You may report side effects to FDA at 1-800-FDA-1088.

How should I store temazepam capsules?

- Store temazepam capsules between 68°F to 77°F (20°C to 25°C).
- Keep temazepam capsules and all medicines out of the reach of children.

General information about the safe and effective use of temazepam capsules.
Medicines are sometimes prescribed for purposes other than those listed in a Medication Guide. Do not use temazepam capsules for a condition for which it was not prescribed. Do not give temazepam capsules to other people, even if they have the same symptoms that you have. It may harm them. You can ask your healthcare provider or pharmacist for information about temazepam capsules that is written for healthcare professionals.

What are the ingredients in temazepam capsules?
Active Ingredient: temazepam
Inactive Ingredients: gelatin, lactose, magnesium stearate, red iron oxide, titanium dioxide
Manufactured by SpecGx LLC
Webster Groves, MO 63119

If you would like more information, call Mallinckrodt Inc. at 1-800-778-7898 or visit www.mallinckrodt.com.

This Medication Guide has been approved by the U.S. Food and Drug Administration

Revised: September 2017

L20T06